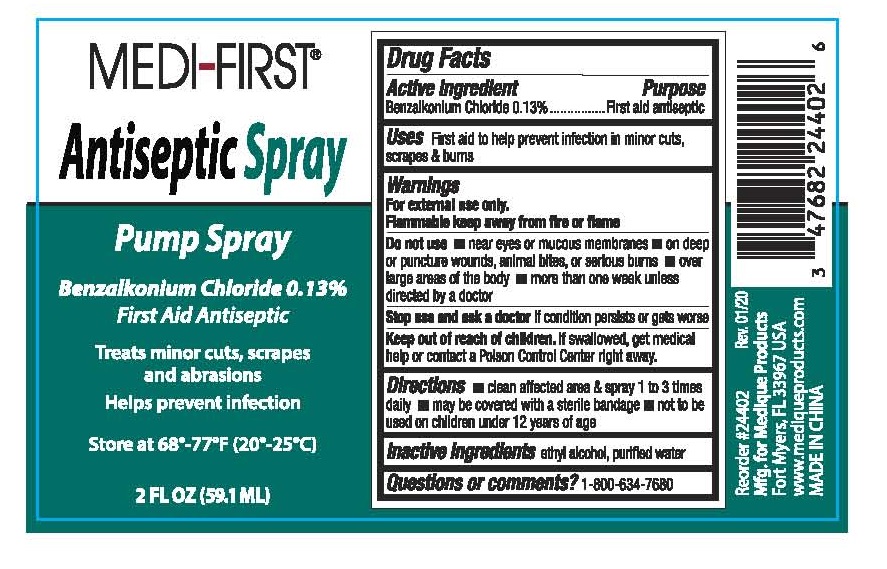 DRUG LABEL: MEDI-FIRST First Aid Antiseptic
NDC: 78495-122 | Form: SPRAY
Manufacturer: Ultra Distributors Inc
Category: otc | Type: HUMAN OTC DRUG LABEL
Date: 20250407

ACTIVE INGREDIENTS: BENZALKONIUM CHLORIDE 1.3 mg/1 mL
INACTIVE INGREDIENTS: WATER; ALCOHOL

78495-122

Active ingredient

Benzalkonium Chloride 0.13%

Purpose

First aid antiseptic

Uses

First aid to help prevent infection in minor cuts, scrapes & burns

Warnings

For external use only.

Flammable, keep away from fire or flame.

Do not use

- near eyes or mucous membranes
- on deep or puncture wounds, animal bites, or serious burns
- over large areas of the body
- more than one week unless directed by a doctor

Stop use and ask a doctor

if condition persists or gets worse

Keep out of reach of children

If swallowed, get medical help or contact a Poison Control Center right away.

Directions

- clean affected area & spray 1 to 3 times daily
- may be covered with a sterile bandage
- not to be used on children under 12 years of age

Inactive ingredients

ethyl alcohol, purified water

Questions or comments?

1-800-634-7680

Treats minor cuts, scrapes and abrasions

Helps prevent infection

Store at 68°-77°F (20°-25°C)